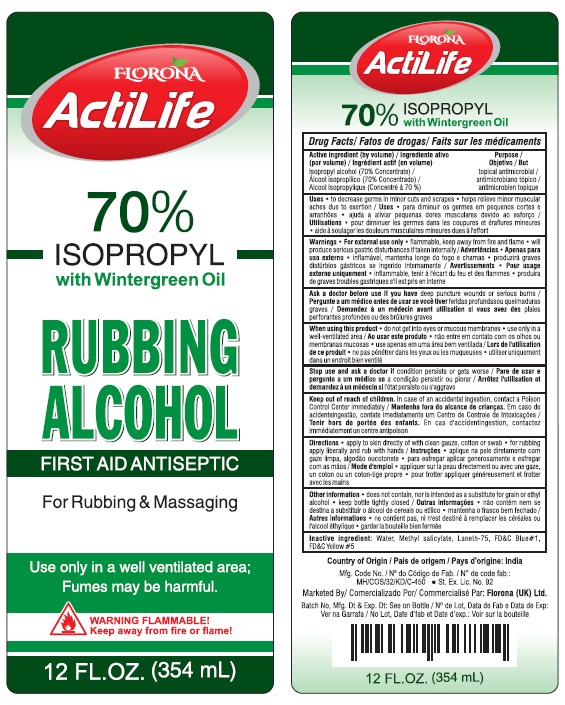 DRUG LABEL: FLORONA ACTILIFE 70% ISOPROPYL RUBBING ALCOHOL WITH WINTERGREEN
NDC: 85891-005 | Form: LIQUID
Manufacturer: SPARROW LIFE CARE PRIVATE LIMITED
Category: otc | Type: HUMAN OTC DRUG LABEL
Date: 20250721

ACTIVE INGREDIENTS: ISOPROPYL ALCOHOL 70 mL/100 mL
INACTIVE INGREDIENTS: WATER; METHYL SALICYLATE; LANETH-75; FD&C BLUE NO. 1; FD&C YELLOW NO. 5

Active Ingredient

Isopropyl alcohol 70%

Purpose

Topical Antimicrobial

Uses

• To decrease germs in minor cuts and scrapes
• Helps relieve minor muscular aches due to exertion

Warnings

- For external use only
- Flammable keep away from fire and flame
- Will produces serious gastric disturbances if taken internally.
- Ask a doctor before use ifyou have deep puncture wounds or serious burns.

When using this product

- do not get into eyes, or mucous membrane
- use only in a well-ventilated area.
- Stop use and ask a doctor ifcondition persist or get worse
- Keep out of reach of children In case of an accidental ingestion, contact a Poison Control Center immediately.

Directions

• Apply to skin directly of with clean gauze, cotton or swab
• For rubbing apply liberally and rub with hands

Other Information

• Does not contain, nor is intended as a substitute for grain or ethyl alcohol
• Keep bottle tightly closed.

Inactive ingredients

Water, Methyl Salicylate, Laneth -75, FD and C Blue #1, FD AND C YELLOW #5